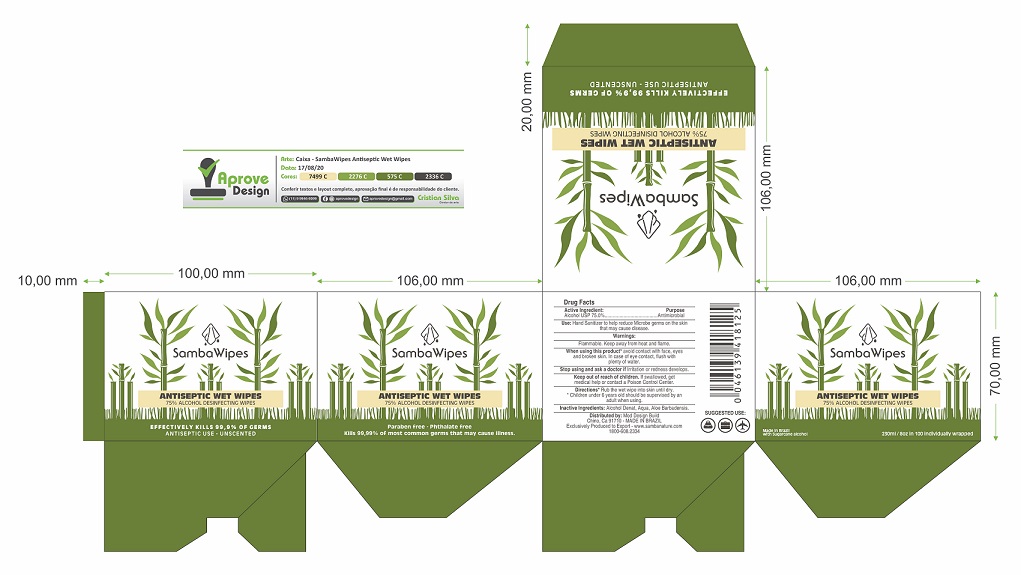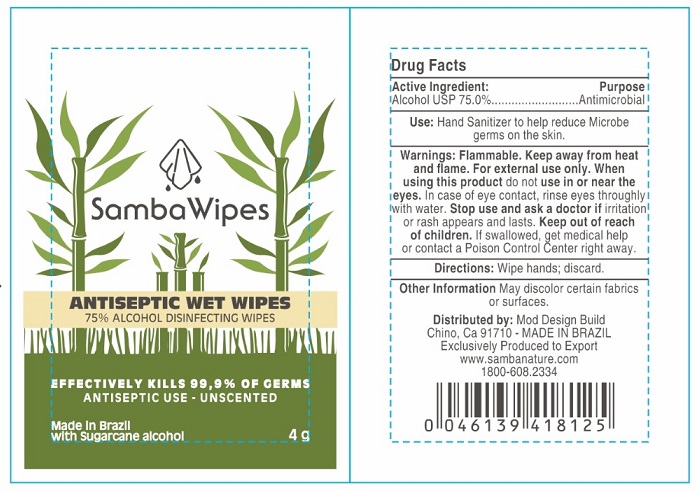 DRUG LABEL: Samba wipes
NDC: 80214-002 | Form: CLOTH
Manufacturer: MOD DESIGN BUILD
Category: otc | Type: HUMAN OTC DRUG LABEL
Date: 20201207

ACTIVE INGREDIENTS: ALCOHOL 75 mL/100 mL
INACTIVE INGREDIENTS: WATER; CARBOMER HOMOPOLYMER, UNSPECIFIED TYPE; GLYCERIN; .ALPHA.-TOCOPHEROL ACETATE; ALOE VERA LEAF

Active Ingredient

Alcohol USP 75.0%

Purpose

Antimicrobial

Use

Hand Sanitizer to help reduce bacteria on the skin that may cause disease.

Warnings

Flammable. Keep away from heat and flame.

For external use only.

When using this product do not use in or near hte eyes. In case of eye contact, rinse eyes throughly with water.

Stop using and ask a doctor if irritation or rash appears and lasts.

Keep out of reach of children. If swallowed, get medical help or contact a Poison Control Center right away.

Directions

- Wipe hands; discard.

Other information

May discolor certain fabrics or surfaces.

Inactive ingredients

Alcohol, Aqua, Aloe Barbadensis Leaf, Parfum, Glycerin, Carbomer, Tocopheryl Acetate, Vitamin E